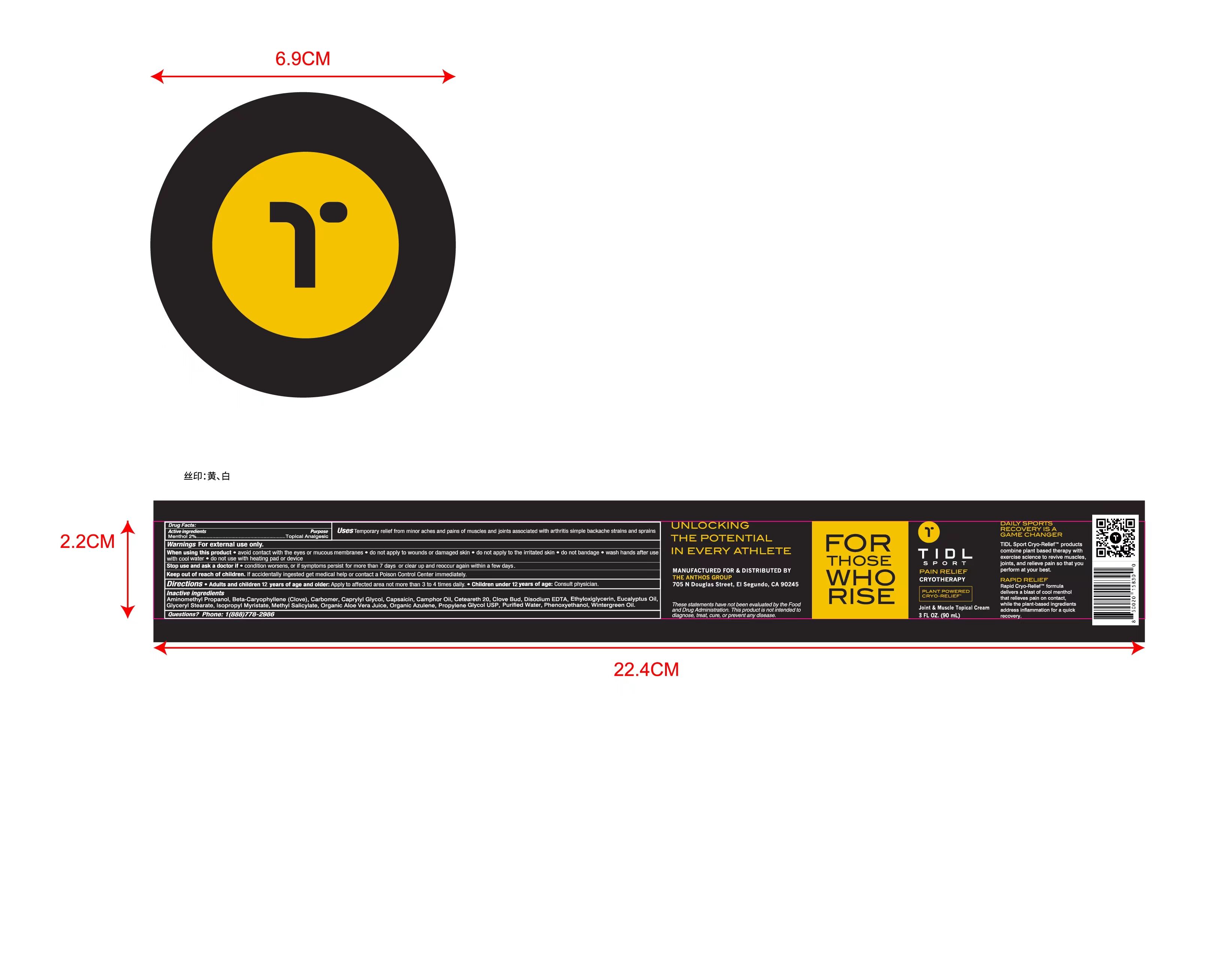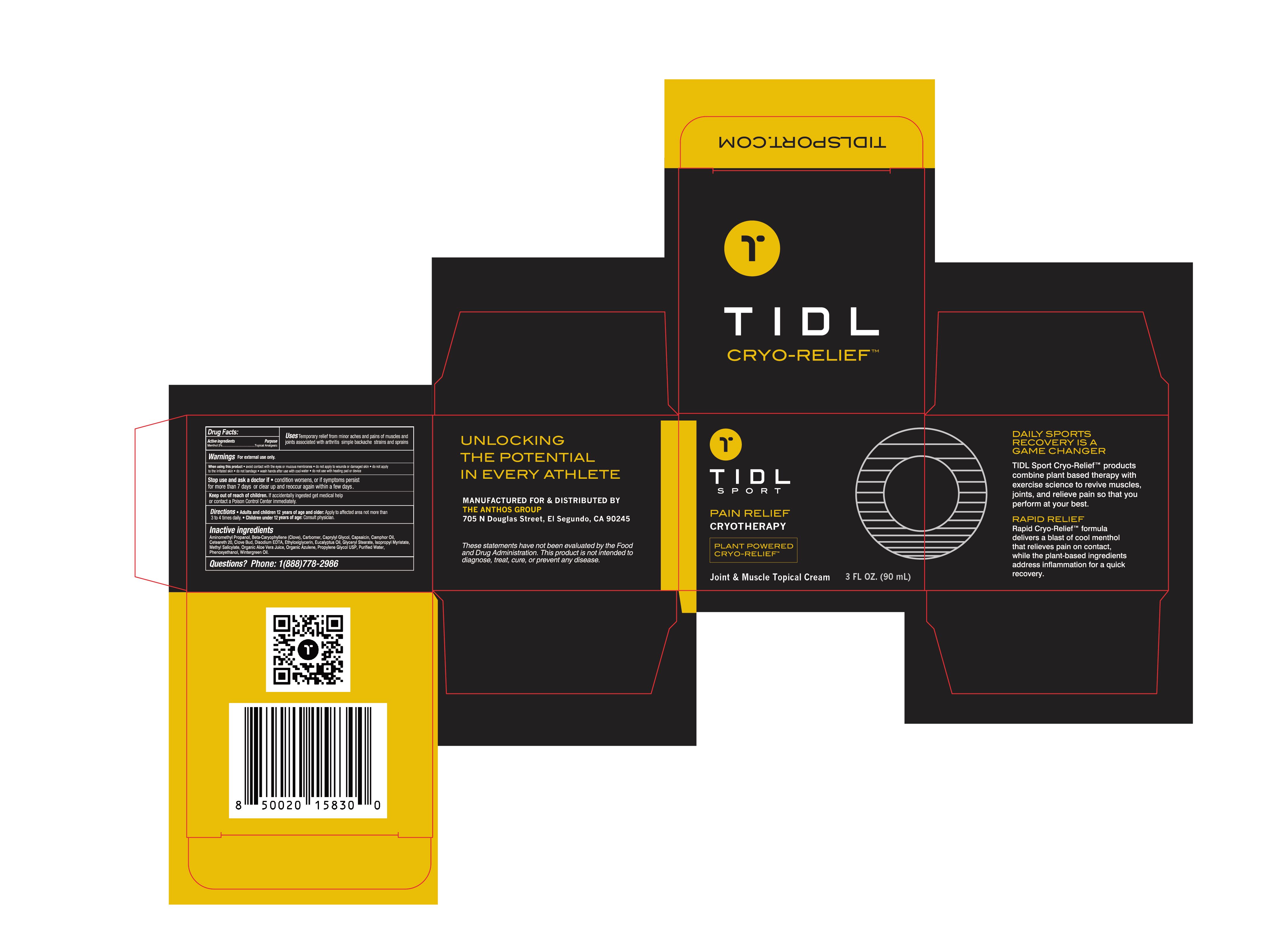 DRUG LABEL: TIDL Sport Cryotherapy Joint   Muscle
NDC: 79740-008 | Form: CREAM
Manufacturer: ANTHOS GROUP, INC, THE
Category: otc | Type: HUMAN OTC DRUG LABEL
Date: 20240220

ACTIVE INGREDIENTS: MENTHOL 2 g/100 mL
INACTIVE INGREDIENTS: EDETATE DISODIUM; ETHYLHEXYLGLYCERIN; 1,2-PROPANEDIOL, 1-BENZOATE; ALOE VERA LEAF; ISOPROPYL MYRISTATE; METHYL SALICYLATE; EUCALYPTUS OIL; WATER; CLOVE; CARYOPHYLLENE; GLYCERYL MONOSTEARATE; PHENOXYETHANOL; CAPRYLYL GLYCOL; CAMPHOR LEAF OIL; CARBOMER HOMOPOLYMER, UNSPECIFIED TYPE; AMINOMETHYLPROPANOL; CAPSAICIN; AZULENE; POLYOXYL 20 CETOSTEARYL ETHER

79740-008 信息更新
TIDL Sport Cryotherapy Joint & Muscle Cream

Active Ingredient(s)

Menthol 2%

Purpose

Topical Analgesic

Use

Temporary relief from minor aches and pains of muscles and joints associated with arthritis simple backache strains and sprains

Warnings

Warnings For external use only.

do not use with heating pad or device.

Stop use and ask a doctor if

condition worsens , or if symptoms persist for more than 7 days or clear up and reoccur again within a few days.

When using this product

avoid contact with the eyes or mucous membranes.

do not apply to wounds or damaged skin.

do not apply to the irritated skin .

do not bandage.

wash hands after use with cool water .

do not use with heating pad or device.

KEEP OUT OF REACH OF CHILDREN

If accidentally ingested get medical help or contact a Poison Control Center immediately

Directions

Adults and children 12 years of age and older: Apply to affected area not more than3 to 4 times daily.

Children under 12 years of age : Consult physician.

Other information

/

Inactive ingredients

Purified Water, Propylene Glycol USP, Organic Aloe Vera Juice, Isopropyl Myristate, Ceteareth 20, Methyl Salicylate, Eucalyptus Oil, Wintergreen Oil, Camphor Oil, Clove Bud, Beta-Caryophyllene（Clove）, Glyceryl Stearate, Phenoxyethanol, Caprylyl Glycol, Ethyloxiglycerin, Disodium EDTA, Capsaicin, Organic Azulene, Carbomer, Aminomethyl Propanol